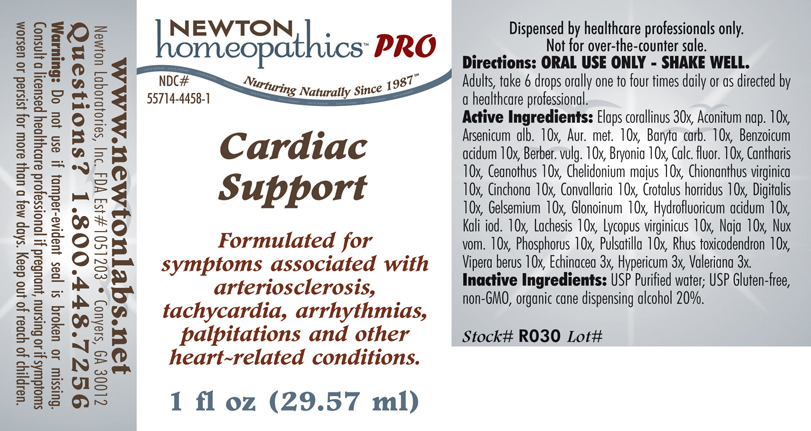 DRUG LABEL: Cardiac Support 
NDC: 55714-4458 | Form: LIQUID
Manufacturer: Newton Laboratories, Inc.
Category: homeopathic | Type: HUMAN PRESCRIPTION DRUG LABEL
Date: 20110601

ACTIVE INGREDIENTS: Micrurus Corallinus Venom 30 [hp_X]/1 mL; Aconitum Napellus 10 [hp_X]/1 mL; Arsenic Trioxide 10 [hp_X]/1 mL; Gold 10 [hp_X]/1 mL; Barium Carbonate 10 [hp_X]/1 mL; Benzoic Acid 10 [hp_X]/1 mL; Berberis Vulgaris Root Bark 10 [hp_X]/1 mL; Bryonia Alba Root 10 [hp_X]/1 mL; Calcium Fluoride 10 [hp_X]/1 mL; Lytta Vesicatoria 10 [hp_X]/1 mL; Ceanothus Americanus Leaf 10 [hp_X]/1 mL; Chelidonium Majus 10 [hp_X]/1 mL; Chionanthus Virginicus Bark 10 [hp_X]/1 mL; Convallaria Majalis 10 [hp_X]/1 mL; Crotalus Horridus Horridus Venom 10 [hp_X]/1 mL; Digitalis 10 [hp_X]/1 mL; Hydrofluoric Acid 10 [hp_X]/1 mL; Gelsemium Sempervirens Root 10 [hp_X]/1 mL; Nitroglycerin 10 [hp_X]/1 mL; Potassium Iodide 10 [hp_X]/1 mL; Lachesis Muta Venom 10 [hp_X]/1 mL; Lycopus Virginicus 10 [hp_X]/1 mL; Naja Naja Venom 10 [hp_X]/1 mL; Strychnos Nux-vomica Seed 10 [hp_X]/1 mL; Phosphorus 10 [hp_X]/1 mL; Pulsatilla Vulgaris 10 [hp_X]/1 mL; Toxicodendron Pubescens Leaf 10 [hp_X]/1 mL; Vipera Berus Venom 10 [hp_X]/1 mL; Echinacea, Unspecified 3 [hp_X]/1 mL; Hypericum Perforatum 3 [hp_X]/1 mL; Valerian 3 [hp_X]/1 mL; Cinchona Officinalis Bark 10 [hp_X]/1 mL
INACTIVE INGREDIENTS: Alcohol

Cardiac Support

PRODUCT NAME & INDICATIONS SECTION

CARDIAC SUPPORT Formulated for symptoms associated with arteriosclerosis, tachycardia, arrhythmias, palpitations and other heart-related conditions.

DIRECTION SECTION

Directions: ORAL USE ONLY - SHAKE WELL. Adults, take 6 drops orally one to four times daily or as directed by a healthcare professional.

ACTIVE INGREDIENT SECTION

Elaps corallinus 30x, Aconitum nap. 10x, Arsenicum alb. 10x, Aur. met.10x, Baryta carb. 10x, Benzoicum acidum 10x, Berber. vulg. 10x, Bryonia 10x, Calc. fluor. 10x, Cantharis 10x, Ceanothus 10x, Chelidonium majus 10x, Chionanthus virginica 10x, Cinchona 10x, Convallaria 10x, Crotalus horridus 10x, Digitalis 10x, Gelsemium 10x, Glonoinum 10x, Hydroflouricum acidum 10x, Kali iod.10x, Lachesis 10x, Lycopus virginicus 10x, Naja 10x, Nux vom. 10x, Phosphorus 10x, Pulsatilla 10x, Rhus toxicodendron 10x, Vipera berus 10x, Echinacea 3x, Hypericum 3x,Valeriana 3x.

PURPOSE SECTION

Formulated for symptoms associated with arteriosclerosis, tachycardia, arrhythmias, palpitations and other heart-related conditions.

INACTIVE INGREDIENT SECTION

Inactive Ingredients: USP Purified Water; USP Gluten-free, non-GMO, organic cane dispensing alcohol 20%.

QUESTIONS? SECTION

www.newtonlabs.net Newton Laboratories, Inc. FDA Est # 1051203 - Conyers, GA 30012
Questions? 1.800.448.7256

WARNINGS SECTION

Warning: Do not use if tamper - evident seal is broken or missing. Consult a licensed healthcare professional if pregnant, nursing or if symptoms worsen or persist for more than a few days. Keep out of reach of children.

OTC - PREGNANCY OR BREAST FEEDING SECTION

Consult a licensed healthcare professional if pregnant or nursing or if symptoms worsen or persist for more than a few days.

OTC - KEEP OUT OF REACH OF CHILDREN SECTION

Keep out of reach of children.